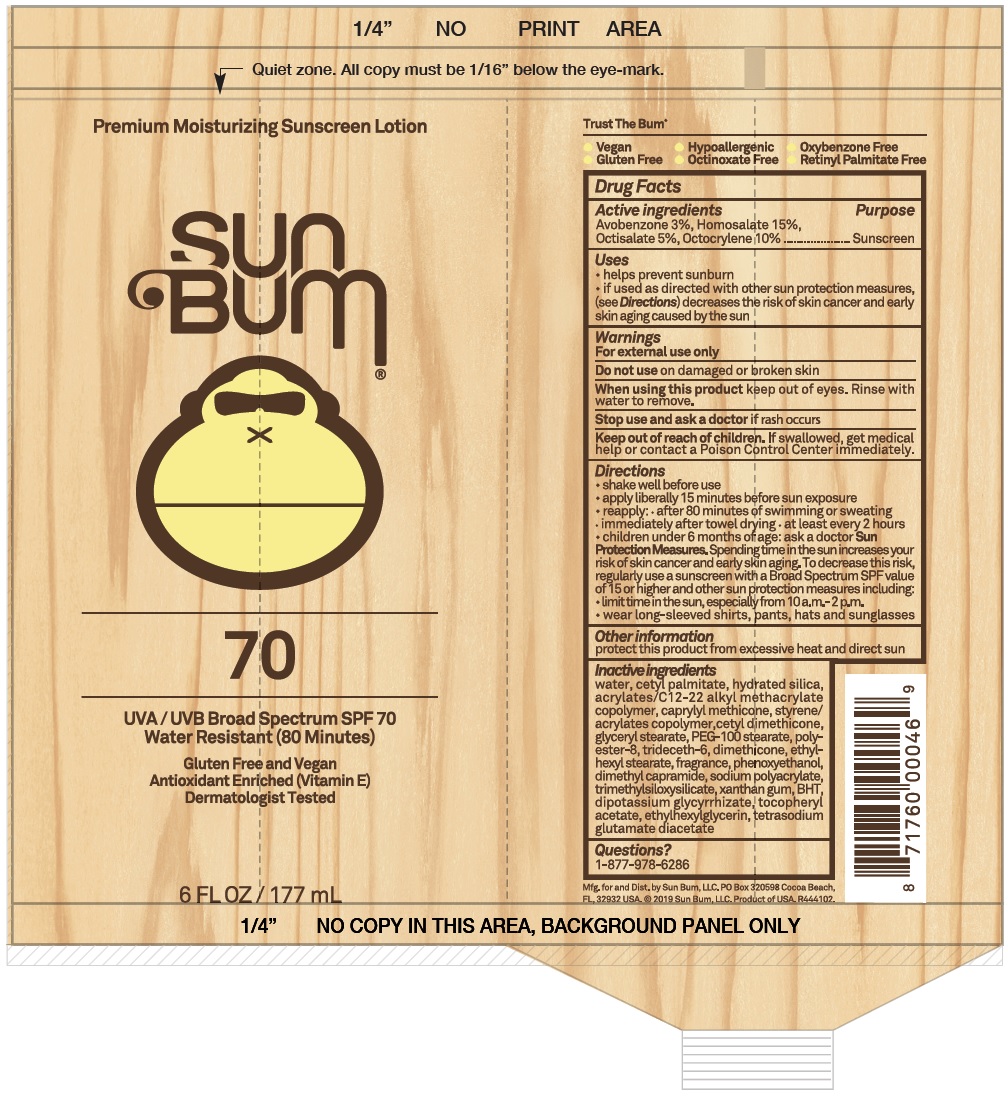 DRUG LABEL: Sun Bum SPF 70 Premium Moisturizing Sunscreen
NDC: 69039-612 | Form: LOTION
Manufacturer: Sun Bum LLC
Category: otc | Type: HUMAN OTC DRUG LABEL
Date: 20220204

ACTIVE INGREDIENTS: AVOBENZONE 30 mg/1 mL; HOMOSALATE 150 mg/1 mL; OCTISALATE 50 mg/1 mL; OCTOCRYLENE 100 mg/1 mL
INACTIVE INGREDIENTS: WATER; CETYL PALMITATE; HYDRATED SILICA; CAPRYLYL TRISILOXANE; GLYCERYL MONOSTEARATE; PEG-100 STEARATE; POLYESTER-8 (1400 MW, CYANODIPHENYLPROPENOYL CAPPED); TRIDECETH-6; DIMETHICONE; ETHYLHEXYL STEARATE; PHENOXYETHANOL; DIMETHYL CAPRAMIDE; XANTHAN GUM; BUTYLATED HYDROXYTOLUENE; GLYCYRRHIZINATE DIPOTASSIUM; .ALPHA.-TOCOPHEROL ACETATE; ETHYLHEXYLGLYCERIN; TETRASODIUM GLUTAMATE DIACETATE

Sun Bum SPF 70 Premium Moisturizing Sunscreen

Active ingredients

Avobenzone 3%, Homosalate 15%, Octisalate 5%, Octocrylene 10%

Purpose

Sunscreen

Warnings

For external use only

Do not use

on damaged or broken skin

When using this product

keep out of eyes. Rinse with water to remove.

Stop use and ask a doctor

if rash occurs

Keep out of reach of children.

If swallowed, get medical help or contact a Poison Control Center immediately.

Directions

- shake well before use
- apply liberally 15 minutes before sun exposure
- reapply: after 80 minutes of swimming or sweating
- immediately after towel drying
- at least every 2 hours
- children under 6 months of age: ask a doctor
- Sun Protection Measures. Spending time in the sun increases your risk of skin cancer and early skin aging. To decrease this risk, regularly use a sunscreen with a Broad Spectrum SPF value of 15 or higher and other sun protection measures including:
- limit time in the sun, especially from 10 a.m. - 2 p.m.
- wear long-sleeved shirts, pants, hats and sunglasses

Other information

protect this product from excessive heat and direct sun

Inactive ingredients

water, cetyl palmitate, hydrated silica, acrylates/C12-22 alkyl methacrylate copolymer, caprylyl methicone, styrene/acrylates copolymer, cetyl dimethicone, glyceryl stearate, PEG-100 stearate, polyester-8, trideceth-6, dimethicone, ethylhexyl stearate, fragrance, phenoxyethanol, dimethyl capramide, sodium polyacrylate, trimethylsiloxysilicate, xanthan gum, BHT, dipotassium glycyrrhizate, tocopheryl acetate, ethylhexyl glycerin, tetrasodium glutamate diacetate

Questions?

1-877-978-6286